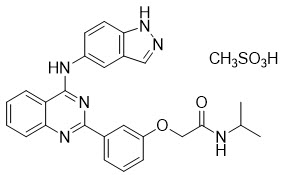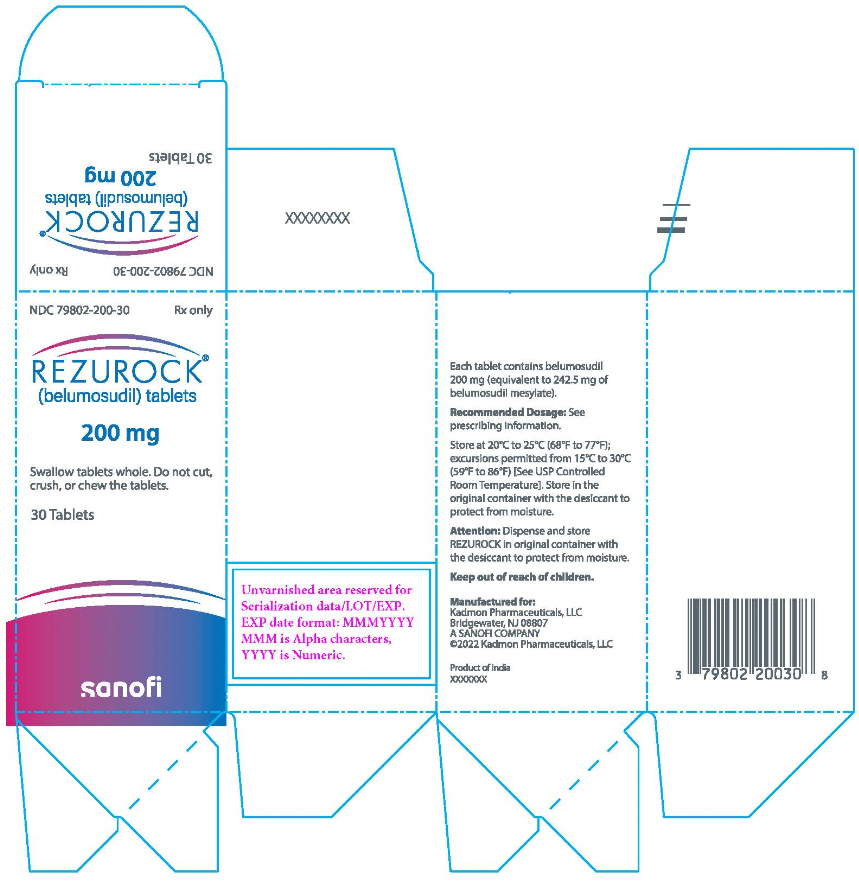 DRUG LABEL: Rezurock
NDC: 79802-200 | Form: TABLET
Manufacturer: Kadmon Pharmaceuticals, LLC
Category: prescription | Type: HUMAN PRESCRIPTION DRUG LABEL
Date: 20260203

ACTIVE INGREDIENTS: BELUMOSUDIL 200 mg/1 1
INACTIVE INGREDIENTS: MICROCRYSTALLINE CELLULOSE; HYPROMELLOSE, UNSPECIFIED; CROSCARMELLOSE SODIUM; SILICON DIOXIDE; MAGNESIUM STEARATE; POLYVINYL ALCOHOL, UNSPECIFIED; TITANIUM DIOXIDE; POLYETHYLENE GLYCOL, UNSPECIFIED; TALC; FERRIC OXIDE YELLOW

HIGHLIGHTS OF PRESCRIBING INFORMATION

These highlights do not include all the information needed to use REZUROCK safely and effectively. See full prescribing information for REZUROCK.
REZUROCK® (belumosudil) tablets, for oral use
Initial U.S. Approval: 2021

1 INDICATIONS AND USAGE

REZUROCK is a kinase inhibitor indicated for the treatment of adult and pediatric patients 12 years and older with chronic graft-versus-host disease (chronic GVHD) after failure of at least two prior lines of systemic therapy. (1)

2 DOSAGE AND ADMINISTRATION

Recommended Dosage: 200 mg taken orally once daily with food. (2.1)

3 DOSAGE FORMS AND STRENGTHS

Tablet: 200 mg. (3)

4 CONTRAINDICATIONS

None. (4)

5 WARNINGS AND PRECAUTIONS

Embryo-Fetal Toxicity: Can cause fetal harm. Advise females of reproductive potential of the potential risk to a fetus and to use effective contraception. (5.1, 8.1, 8.3)

6 ADVERSE REACTIONS

The most common (≥20%) adverse reactions, including laboratory abnormalities, are infections, asthenia, nausea, diarrhea, dyspnea, cough, edema, hemorrhage, abdominal pain, musculoskeletal pain, headache, phosphate decreased, gamma glutamyl transferase increased, lymphocytes decreased, and hypertension. (6.1)

To report SUSPECTED ADVERSE REACTIONS, contact Kadmon Pharmaceuticals, LLC at 1-800-633-1610 or FDA at 1-800-FDA-1088 or www.fda.gov/medwatch.

7 DRUG INTERACTIONS

- Strong CYP3A Inducers: Increase REZUROCK dosage to 200 mg twice daily. (7.1, 2.3)
- Proton Pump Inhibitors: Increase REZUROCK dosage to 200 mg twice daily. (7.1, 2.3)
- BCRP Substrates: Avoid concomitant use with drugs that are BCRP substrates where possible. If used together, monitor patients more frequently for adverse reactions and decrease the substrates dosage(s) in accordance with the respective Prescribing Information. (7.2)
- OATP1B1 Substrates: If used together, monitor patients more frequently for adverse reactions and decrease the substrates dosage(s) in accordance with the respective Prescribing Information. (7.2)
- Certain CYP1A2, CYP3A, P-gp or UGT1A1 Substrates: Avoid concomitant use with these substrates for which minimal concentration changes may lead to serious toxicities. If concomitant use cannot be avoided, decrease the substrates dosage(s) in accordance with the respective Prescribing Information. (7.2)

8 USE IN SPECIFIC POPULATIONS

- Lactation: Advise not to breastfeed. (8.2)
- Moderate or Severe Hepatic Impairment: Avoid use of REZUROCK in patients with moderate or severe hepatic impairment. (2.4, 8.7)

FULL PRESCRIBING INFORMATION

1 INDICATIONS AND USAGE

REZUROCK is indicated for the treatment of adult and pediatric patients 12 years and older with chronic graft-versus-host disease (chronic GVHD) after failure of at least two prior lines of systemic therapy.

2 DOSAGE AND ADMINISTRATION

2.1 Recommended Dosage

The recommended dose of REZUROCK is 200 mg given orally once daily until progression of chronic GVHD that requires new systemic therapy.

Instruct the patient on the following:

- Swallow REZUROCK tablets whole. Do not cut, crush, or chew tablets.
- Take REZUROCK with a meal at approximately the same time each day [see Clinical Pharmacology (12.3)].
- If a dose of REZUROCK is missed, instruct the patient to not take extra doses to make up the missed dose.

Treatment with REZUROCK has not been studied in patients with pre-existing severe renal impairment. For patients with pre-existing severe renal impairment, consider the risks and potential benefits before initiating treatment with REZUROCK [see Clinical Pharmacology (12.3)].

2.2 Dosage Modifications for Adverse Reactions

Monitor total bilirubin, aspartate aminotransferase (AST), and alanine aminotransferase (ALT) at least monthly.

Modify the REZUROCK dosage for adverse reactions as per Table 1.

Table 1: Recommended Dosage Modifications for REZUROCK for Adverse Reactions
Adverse Reaction | Severity [Based on CTCAE v 4.03] | REZUROCK Dosage Modifications
Hepatotoxicity [see Adverse Reactions (6.1)] | Grade 3 AST or ALT (5× to 20× ULN) or Grade 2 bilirubin (1.5× to 3× ULN) | Hold REZUROCK until recovery of bilirubin, AST and ALT to Grade 0–1, then resume REZUROCK at the recommended dose.
Hepatotoxicity [see Adverse Reactions (6.1)] | Grade 4 AST or ALT (more than 20× ULN) or Grade ≥3 bilirubin (more than 3× ULN) | Discontinue REZUROCK permanently.
Other adverse reactions [see Adverse Reactions (6.1)] | Grade 3 | Hold REZUROCK until recovery to Grade 0–1, then resume REZUROCK at the recommended dose level.
Other adverse reactions [see Adverse Reactions (6.1)] | Grade 4 | Discontinue REZUROCK permanently.

2.3 Dosage Modification Due to Drug Interactions

Strong CYP3A Inducers

Increase the dosage of REZUROCK to 200 mg twice daily when coadministered with strong CYP3A inducers [see Drug Interactions (7.1)].

Proton Pump Inhibitors

Increase the dosage of REZUROCK to 200 mg twice daily when coadministered with proton pump inhibitors [see Drug Interactions (7.1)].

2.4 Recommended Dosage in Patients with Hepatic Impairment

Avoid use in patients with moderate hepatic impairment (Child-Pugh B) or severe hepatic impairment (Child-Pugh C) without liver GVHD [see Use in Specific Populations (8.7), Clinical Pharmacology (12.3)].

No dosage adjustment is recommended when administering REZUROCK to patients with mild hepatic impairment [see Use in Specific Populations (8.7), Clinical Pharmacology (12.3)].

3 DOSAGE FORMS AND STRENGTHS

Each 200 mg belumosudil tablet is a pale yellow film-coated oblong tablet debossed with "KDM" on one side and "200" on the other side.

4 CONTRAINDICATIONS

None.

5 WARNINGS AND PRECAUTIONS

5.1 Embryo-Fetal Toxicity

Based on findings in animals and its mechanism of action, REZUROCK can cause fetal harm when administered to a pregnant woman. In animal reproduction studies, administration of belumosudil to pregnant rats and rabbits during the period of organogenesis caused adverse developmental outcomes including embryo-fetal mortality and malformations at maternal exposures (AUC) less than those in patients at the recommended dose. Advise pregnant women of the potential risk to a fetus. Advise females of reproductive potential and males with female partners of reproductive potential to use effective contraception during treatment with REZUROCK and for one week after the last dose [see Use in Specific Populations (8.1, 8.3), Nonclinical Toxicology (13.1)].

6 ADVERSE REACTIONS

6.1 Clinical Trial Experience

Because clinical trials are conducted under widely variable conditions, adverse reaction rates observed in clinical trials of a drug cannot be directly compared with rates of clinical trials of another drug and may not reflect the rates observed in practice.

Chronic Graft versus Host Disease

In two clinical trials (Study KD025-213 and Study KD025-208), 83 adult patients with chronic GVHD were treated with REZUROCK 200 mg once daily [see Clinical Studies (14.1)]. The median duration of treatment was 9.2 months (range 0.5 to 44.7 months).

Fatal adverse reaction was reported in one patient with severe nausea, vomiting, diarrhea and multi-organ failure.

Permanent discontinuation of REZUROCK due to adverse reactions occurred in 18% of patients. The adverse reactions which resulted in permanent discontinuation of REZUROCK in >3% of patients included nausea (4%). Adverse reactions leading to dose interruption occurred in 29% of patients. The adverse reactions leading to dose interruption in ≥2% were infections (11%), diarrhea (4%), and asthenia, dyspnea, hemorrhage, hypotension, liver function test abnormal, nausea, pyrexia, edema, and renal failure with (2% each).

The most common (≥20%) adverse reactions, including laboratory abnormalities, were infections, asthenia, nausea, diarrhea, dyspnea, cough, edema, hemorrhage, abdominal pain, musculoskeletal pain, headache, phosphate decreased, gamma glutamyl transferase increased, lymphocytes decreased, and hypertension.

Table 2 summarizes the nonlaboratory adverse reactions.

Table 2: Nonlaboratory Adverse Reactions in ≥10% Patients with Chronic GVHD Treated with REZUROCK
Adverse Reaction | REZUROCK 200 mg once daily (N=83)
Adverse Reaction | All Grades (%) | Grades 3–4 (%)
Infections and infestations
Infection (pathogen not specified) [infection with an unspecified pathogen includes acute sinusitis, device related infection, ear infection, folliculitis, gastroenteritis, gastrointestinal infection, hordeolum, infectious colitis, lung infection, skin infection, tooth infection, urinary tract infection, wound infection, upper respiratory tract infection, pneumonia, conjunctivitis, sinusitis, respiratory tract infection, bronchitis, sepsis, septic shock.] | 53 | 16
Viral infection [includes influenza, rhinovirus infection, gastroenteritis viral, viral upper respiratory tract infection, bronchitis viral, Epstein-Barr viremia, Epstein-Barr virus infection, parainfluenzae virus infection, Varicella zoster virus infection, viral infection.] | 19 | 4
Bacterial infection [includes cellulitis, Helicobacter infection, Staphylococcal bacteremia, catheter site cellulitis, Clostridium difficile colitis, Escherichia urinary tract infection, gastroenteritis Escherichia coli, Pseudomonas infection, urinary tract infection bacterial.] | 16 | 4
General disorders and administration site conditions
Asthenia [includes fatigue, asthenia, malaise.] | 46 | 4
Edema [includes edema peripheral, generalized edema, face edema, localized edema, edema.] | 27 | 1
Pyrexia | 18 | 1
Gastrointestinal
Nausea [includes nausea, vomiting.] | 42 | 4
Diarrhea | 35 | 5
Abdominal pain [includes abdominal pain, abdominal pain upper, abdominal pain lower.] | 22 | 1
Dysphagia | 16 | 0
Respiratory, thoracic and mediastinal
Dyspnea [includes dyspnea, dyspnea exertional, apnea, orthopnea, sleep apnea syndrome.] | 33 | 5
Cough [includes cough, productive cough.] | 30 | 0
Nasal congestion | 12 | 0
Vascular
Hemorrhage [includes contusion, hematoma, epistaxis, increased tendency to bruise, conjunctival hemorrhage, hematochezia, mouth hemorrhage, catheter site hemorrhage, hematuria, hemothorax, purpura.] | 23 | 5
Hypertension | 21 | 7
Musculoskeletal and connective tissue
Musculoskeletal pain [includes pain in extremity, back pain, flank pain, limb discomfort, musculoskeletal chest pain, neck pain, musculoskeletal pain.] | 22 | 4
Muscle spasm | 17 | 0
Arthralgia | 15 | 2
Nervous system
Headache [includes headache, migraine.] | 21 | 0
Metabolism and nutrition
Decreased appetite | 17 | 1
Skin and subcutaneous
Rash [includes rash, rash maculo-papular, rash erythematous, rash generalized, dermatitis exfoliative.] | 12 | 0
Pruritus [includes pruritus, pruritus generalized.] | 11 | 0

Table 3 summarizes the laboratory abnormalities in REZUROCK.

Table 3: Selected Laboratory Abnormalities in Patients with Chronic GVHD Treated with REZUROCK
 | REZUROCK 200 mg once daily
 | Grade 0–1 Baseline | Grade 2–4 Max Post | Grade 3–4 Max Post
Parameter | (N) | (%) | (%)
Chemistry
Phosphate decreased | 76 | 28 | 7
Gamma Glutamyl Transferase increased | 47 | 21 | 11
Calcium decreased | 82 | 12 | 1
Alkaline Phosphatase increased | 80 | 9 | 0
Potassium increased | 82 | 7 | 1
Alanine Aminotransferase increased | 83 | 7 | 2
Creatinine increased | 83 | 4 | 0
Hematology
Lymphocytes decreased | 62 | 29 | 13
Hemoglobin decreased | 79 | 11 | 1
Platelets decreased | 82 | 10 | 5
Neutrophil Count decreased | 83 | 8 | 4

7 DRUG INTERACTIONS

7.1 Effect of Other Drugs on REZUROCK

Proton Pump Inhibitors

Belumosudil exhibits pH-dependent solubility. Concomitant use of REZUROCK with proton pump inhibitors decreases belumosudil exposure [see Clinical Pharmacology (12.3)], which may reduce the efficacy of REZUROCK. Increase the dosage of REZUROCK when used concomitantly with proton pump inhibitors [see Dosage and Administration (2.3)].

Strong CYP3A Inducers

Belumosudil is a CYP3A substrate. Concomitant use of REZUROCK with strong CYP3A inducers decreases belumosudil exposure [see Clinical Pharmacology (12.3)], which may reduce the efficacy of REZUROCK. Increase the dosage of REZUROCK when used concomitantly with strong CYP3A inducers [see Dosage and Administration (2.3)].

7.2 Effect of REZUROCK on Other Drugs

BCRP and OATP1B1 Substrates

Avoid concomitant use with drugs that are BCRP substrates where possible. If used together, monitor patients more frequently for adverse reactions and decrease the BCRP substrates dosage(s) in accordance with the respective Prescribing Information.

Belumosudil is a BCRP inhibitor. Concomitant use of REZUROCK with BCRP substrates increases their plasma concentrations [see Clinical Pharmacology (12.3)], which may increase the risk of adverse reactions related to these substrates.

Belumosudil is an OATP1B1 inhibitor. Concomitant use of REZUROCK with OATP1B1 substrates may increase their plasma concentrations. Monitor patients more frequently for adverse reactions of these substrates and decrease the OATP1B1 substrates dosage(s) in accordance with the respective Prescribing Information [see Clinical Pharmacology (12.3)].

Certain CYP1A2 Substrates

Avoid concomitant use of REZUROCK with drugs that are sensitive CYP1A2 substrates, for which minimal concentration changes may lead to serious toxicities. If concomitant use cannot be avoided, decrease the CYP1A2 substrate dosage(s) in accordance with the respective Prescribing Information.

Belumosudil is a CYP1A2 inhibitor. Concomitant use of REZUROCK with sensitive CYP1A2 substrates (e.g., caffeine) is predicted to increase CYP1A2 substrate exposure [see Clinical Pharmacology (12.3)], which may increase the risk of adverse reactions related to these substrates.

Certain CYP3A Substrates

Avoid concomitant use of REZUROCK with drugs that are sensitive CYP3A substrates, for which minimal concentration changes may lead to serious toxicities. If concomitant use cannot be avoided, decrease the CYP3A substrate dosage(s) in accordance with the respective Prescribing Information.

Belumosudil is a CYP3A inhibitor. Concomitant use of REZUROCK with sensitive CYP3A substrates (e.g., midazolam) is predicted to increase CYP3A substrate exposure [see Clinical Pharmacology (12.3)], which may increase the risk of adverse reactions related to these substrates.

Certain UGT1A1 Substrates

Avoid concomitant use of REZUROCK with drugs that are UGT1A1 substrates, for which minimal concentration changes may lead to serious toxicities. If concomitant use cannot be avoided, decrease the UGT1A1 substrates dosage(s) in accordance with the respective Prescribing Information.

Belumosudil is a UGT1A1 inhibitor. Concomitant use of REZUROCK with a UGT1A1 substrate decreased plasma concentrations of the glucuronide metabolite of the UGT1A1 substrate [see Clinical Pharmacology (12.3)]. Concomitant use of belumosudil with other UGT1A1 substrates may increase their plasma concentrations, which may increase the risk of adverse reactions related to these substrates.

Certain P-gp Substrates

Avoid concomitant use of REZUROCK with drugs that are P-gp substrates, for which minimal concentration changes may lead to serious toxicities. If concomitant use cannot be avoided, decrease the P-gp substrates dosage(s) in accordance with the respective Prescribing Information.

Belumosudil is a P-gp inhibitor. Concomitant use of REZUROCK with P-gp substrates increased their plasma concentrations [see Clinical Pharmacology (12.3)], which may increase the risk of adverse reactions related to these substrates.

8 USE IN SPECIFIC POPULATIONS

8.1 Pregnancy

Risk Summary

Based on findings from animal studies and the mechanism of action [see Clinical Pharmacology (12.1)], REZUROCK can cause fetal harm when administered to pregnant women. There are no available human data on REZUROCK use in pregnant women to evaluate for a drug-associated risk. In animal reproduction studies, administration of belumosudil to pregnant rats and rabbits during the period of organogenesis resulted in adverse developmental outcomes, including alterations to growth, embryo-fetal mortality, and embryo-fetal malformations at maternal exposures (AUC) approximately ≥1.4 (rat) and ≥0.08 (rabbit) times the human exposure (AUC) at the recommended dose (see Data). Advise pregnant women and females of reproductive potential of the potential risk to the fetus.

In the U.S. general population, the estimated background risk of major birth defects and miscarriage in clinically recognized pregnancies is 2 to 4% and 15 to 20%, respectively.

Data

Animal data

Embryo-fetal development studies were conducted in rats with administration of belumosudil to pregnant animals during the period of organogenesis at oral doses of 25, 50, 150, and 300 mg/kg/day in a pilot study and doses of 15, 50, and 150 mg/kg/day in a pivotal study. In the pilot study, maternal toxicity and embryo-fetal developmental effects were observed. Maternal toxicity (reduced body weight gain) occurred at 150 and 300 mg/kg/day doses. Increased post-implantation loss occurred at 50 and 300 mg/kg/day. Fetal-malformations were observed at ≥50 mg/kg/day and included absence of anus and tail, omphalocele, and dome shaped head. The exposure (AUC) at 50 mg/kg/day in rats is approximately 1.4 times the human exposure at the recommended dose of 200 mg.

In an embryo-fetal developmental study in rabbits, pregnant animals administered oral doses of belumosudil at 50, 125, and 225 mg/kg/day during the period of organogenesis resulted in maternal toxicity and embryo-fetal developmental effects. Maternal toxicity (body weight loss and mortality) was observed at doses ≥125 mg/kg/day. Embryo-fetal effects were observed at doses ≥50 mg/kg/day and included spontaneous abortion, increased post-implantation loss, decreased percentage of live fetuses, malformations, and decreased fetal body weight. Malformations included those in the tail (short), ribs (branched, fused or deformed), sternebrae (fused), and neural arches (fused, misaligned, and deformed). The exposure (AUC) at 50 mg/kg/day in rabbits is approximately 0.08 times the human exposure at the recommended dose of 200 mg.

8.2 Lactation

Risk Summary

There are no data available on the presence of belumosudil or its metabolites in human milk or the effects on the breastfed child, or milk production. Because of the potential for serious adverse reactions from belumosudil in the breastfed child, advise lactating women not to breastfeed during treatment with REZUROCK and for one week after the last dose.

8.3 Females and Males of Reproductive Potential

REZUROCK can cause fetal harm when administered to a pregnant woman [see Use in Specific Populations (8.1)].

Pregnancy Testing

Verify the pregnancy status of females of reproductive potential prior to initiating treatment with REZUROCK.

Contraception

Females

Advise females of reproductive potential to use effective contraception during treatment with REZUROCK and for one week after the last dose of REZUROCK. If this drug is used during pregnancy or if the patient becomes pregnant while taking this drug, the patient should be informed of the potential hazard to a fetus.

Males

Advise males with female partners of reproductive potential to use effective contraception during treatment with REZUROCK and for one week after the last dose of REZUROCK.

Infertility

Females

Based on findings from rats, REZUROCK may impair female fertility [see Nonclinical Toxicology (13.1)].

Males

Based on findings from rats and dogs, REZUROCK may impair male fertility [see Nonclinical Toxicology (13.1)].

8.4 Pediatric Use

The safety and effectiveness of REZUROCK have been established in pediatric patients 12 years and older. Use of REZUROCK in this age group is supported by evidence from adequate and well-controlled studies of REZUROCK in adults with additional population pharmacokinetic data demonstrating that age and body weight had no clinically meaningful effect on the pharmacokinetics of drug substance, that the exposure of drug substance is expected to be similar between adults and pediatric patients age 12 years and older, and that the course of disease is sufficiently similar in adult and pediatric patients to allow extrapolation of data in adults to pediatric patients.

The safety and effectiveness of REZUROCK in pediatric patients less than 12 years old have not been established.

8.5 Geriatric Use

Of the 186 patients with chronic GVHD in clinical studies of REZUROCK, 26% were 65 years and older. No clinically meaningful differences in safety or effectiveness of REZUROCK were observed in comparison to younger patients.

8.6 Renal Impairment

Treatment with REZUROCK has not been studied in patients with pre-existing severe renal impairment. For patients with pre-existing severe renal impairment, consider the risks and potential benefits before initiating treatment with REZUROCK [see Dosage and Administration (2.1) and Clinical Pharmacology (12.3)].

8.7 Hepatic Impairment

Avoid use in patients with moderate hepatic impairment (Child-Pugh B) or severe hepatic impairment (Child-Pugh C) without liver GVHD [see Dosage and Administration (2.4), Clinical Pharmacology (12.3)].

No dosage adjustment is recommended for patients with mild hepatic impairment (Child-Pugh A) [see Dosage and Administration (2.4), Clinical Pharmacology (12.3)].

11 DESCRIPTION

Belumosudil is a kinase inhibitor. The active pharmaceutical ingredient is belumosudil mesylate with the molecular formula C27H28N6O5S and the molecular weight is 548.62 g/mol. The chemical name for belumosudil mesylate is 2-{3-[4-(1H-indazol-5-ylamino)-2-quinazolinyl]phenoxy}-N-(propan-2-yl) acetamide methanesulfonate (1:1). The chemical structure is as follows:

Belumosudil mesylate is a yellow powder that is practically insoluble in water, slightly soluble in methanol and DMF and soluble in DMSO.

REZUROCK tablets are for oral administration. Each tablet contains 200 mg of the free base equivalent to 242.5 mg of belumosudil mesylate. The tablet also contains the following inactive ingredients: colloidal silicon dioxide, croscarmellose sodium, hypromellose, magnesium stearate, and microcrystalline cellulose.

The tablet film consists of polyethylene glycol, polyvinyl alcohol, talc, titanium dioxide and yellow iron oxide.

12 CLINICAL PHARMACOLOGY

12.1 Mechanism of Action

Belumosudil is an inhibitor of rho-associated, coiled-coil containing protein kinase (ROCK) which inhibits ROCK2 and ROCK1 with IC50 values of approximately 100 nM and 3 µM, respectively. Belumosudil down-regulated proinflammatory responses via regulation of STAT3/STAT5 phosphorylation and shifting Th17/Treg balance in ex-vivo or in vitro-human T cell assays. Belumosudil also inhibited aberrant pro-fibrotic signaling, in vitro. In vivo, belumosudil demonstrated activity in animal models of chronic GVHD.

12.2 Pharmacodynamics

Belumosudil exposure-response relationships and the time course of pharmacodynamic response are not established.

Cardiac Electrophysiology

At 2.4 times the maximum exposure for approved recommended dose, REZUROCK does not prolong the QT interval to any clinically relevant extent.

12.3 Pharmacokinetics

The following pharmacokinetic parameters are presented for chronic GVHD patients administered belumosudil 200 mg once daily, unless otherwise specified. The mean (% coefficient of variation, %CV) steady-state AUC and Cmax of belumosudil was 22,700 (48%) h∙ng/mL and 2390 (44%) ng/mL, respectively. Belumosudil Cmax and AUC increased in an approximately proportional manner over a dosage range of 200 and 400 mg (1 to 2 times once daily recommended dosage). The accumulation ratio of belumosudil was 1.4.

Absorption

Median Tmax of belumosudil at steady state was 1.26 to 2.53 hours following administration of 200 mg once daily or twice daily in patients. The mean (%CV) bioavailability was 64% (17%) following a single belumosudil dose in healthy subjects.

Effect of Food

Belumosudil Cmax and AUC increased 2.2 times and 2 times, respectively, following administration of a single belumosudil dose with a high-fat and high-calorie meal (800 to 1,000 calories with approximately 50% of total caloric content of the meal from fat) compared to the fasted state in healthy subjects. Median Tmax was delayed 0.5 hours.

Distribution

The geometric mean volume of distribution after a single dose of belumosudil in healthy subjects was 184 L (geo CV% 67.7%).

Belumosudil binding to human serum albumin and human α1-acid glycoprotein was 99.9% and 98.6%, respectively, in vitro.

Elimination

The mean (%CV) elimination half-life of belumosudil was 19 hours (39%), and clearance was 9.83 L/hours (46%) in patients.

Metabolism

Belumosudil is primarily metabolized by CYP3A and to a lesser extent by CYP2C8, CYP2D6, and UGT1A9, in vitro.

Excretion

Following a single oral dose of radiolabeled belumosudil in healthy subjects, 85% of radioactivity was recovered in feces (30% as unchanged) and less than 5% in urine.

Specific Populations

No clinically significant differences in belumosudil pharmacokinetics were observed with regard to age (18 to 77 years), sex, weight (38.6 to 143 kg), or mild to moderate renal impairment (eGFR ≥60 and <90 mL/min/1.72m^2 to eGFR ≥30 and <60 mL/min/1.72m^2). The effect of severe renal impairment on the pharmacokinetics of belumosudil has not been studied.

Patients with Hepatic Impairment

Following a single 200 mg dose of belumosudil, changes in belumosudil exposure in subjects with varying degrees of hepatic impairment based on Child-Pugh score without liver GVHD relative to subjects with normal hepatic function is shown in Table 4.

Table 4: Effect of Varying Degrees of Hepatic Impairment on Belumosudil Exposure
Hepatic Impairment Category | Changes in Belumosudil Exposure in Subjects with Hepatic Impairment Compared to Subjects with Normal Hepatic Function
Hepatic Impairment Category | Total (Free + Bound) Concentrations |  | Free Concentrations
Hepatic Impairment Category | Cmax | AUC | Cmax | AUC
Mild (Child-Pugh A) | 1.2-fold increase | 1.4-fold increase | 14% decrease | 19% decrease
Moderate (Child-Pugh B) | 6% decrease | 1.5-fold increase | 12% decrease | 1.4-fold increase
Severe (Child-Pugh C) | 1.3-fold increase | 4.2-fold increase | 5.4-fold increase | 16-fold increase

Drug Interaction Studies

Clinical Studies and Model-Informed Approaches

Proton Pump Inhibitors: Concomitant use of rabeprazole decreased belumosudil Cmax by 87% and AUC by 80%, and omeprazole decreased belumosudil Cmax by 68% and AUC by 47% in healthy subjects.

Strong Cytochrome P450 (CYP) 3A Inhibitors: There was no clinically meaningful effect on belumosudil exposure when used concomitantly with itraconazole (strong CYP3A inhibitor) in healthy subjects.

Strong CYP3A Inducers: Concomitant use of rifampin (strong CYP3A inducer) decreased belumosudil Cmax by 59% and AUC by 72% in healthy subjects.

Moderate CYP3A Inducers: Concomitant use of efavirenz (moderate CYP3A inducer) is predicted to decrease belumosudil Cmax by 19% and AUC by 35% in healthy subjects.

CYP1A2 Substrates: Concomitant use of belumosudil is predicted to increase caffeine (sensitive CYP1A2 substrate) Cmax and AUC approximately 1.1- and 1.6-fold, respectively.

CYP3A Substrates: Concomitant use of belumosudil is predicted to increase midazolam (sensitive CYP3A substrate) Cmax and AUC approximately 1.3- and 1.7-fold, respectively.

UGT1A1 Substrates: Concomitant use of belumosudil did not have clinically significant effect on the exposure of raltegravir (UGT1A1 substrate), but decreased raltegravir glucuronide (metabolite formed via the UGT1A1 pathway) Cmax by 42% and AUC by 40%.

BCRP/OATP1B1 Substrates: Concomitant use of belumosudil increased rosuvastatin (BCRP and OATP1B1 substrate) Cmax and AUC by 3.6- and 4.6-fold, respectively.

P-glycoprotein (P-gp) Substrates: Concomitant use of belumosudil increased dabigatran (P-gp substrate) Cmax and AUC by 2-fold.

Other drugs: Concomitant use of belumosudil is not predicted to have clinically significant effects on the exposure of (S)-warfarin (CYP2C9 substrate), omeprazole (CYP2C19 substrate), and CYP2C8 substrates that are not an OATP1B1 substrate.

In Vitro Studies

UDP-Glucuronosyltransferase (UGT): Belumosudil is an inhibitor of UGT1A9.

Transporter Systems: Belumosudil is a substrate of P-gp.

13 NONCLINICAL TOXICOLOGY

13.1 Carcinogenesis, Mutagenesis, Impairment of Fertility

Carcinogenesis

Belumosudil did not result in any carcinogenic effect in a 6-month CByB6F1-Tg (HRAS)2Jic hemizygous mouse study at oral doses up to 15 mg/kg/day in female and 30 mg/kg/day in male mice.

Mutagenesis

Belumosudil was not genotoxic in an in vitro bacterial mutagenicity (Ames) assay, in vitro chromosome aberration assay in human peripheral blood lymphocytes (HPBL) or an in vivo rat bone marrow micronucleus assay.

Impairment of Fertility

In a combined male and female rat fertility and early embryonic development study, belumosudil-treated male animals were mated with untreated females, or untreated males were mated with belumosudil-treated females. Belumosudil was administered orally at doses of 50, 150 or 275 mg/kg/day to male rats 70 days prior to and throughout the mating period, and to female rats 14 days prior to mating and up to Gestation Day 7. At the dose of 275 mg/kg/day, adverse findings in female rats (treated with belumosudil or untreated but mated with treated males) regarding early embryonic development included increased pre- or post-implantation loss and decreased number of viable embryos. Administration of belumosudil to male rats at a dose of 275 mg/kg/day resulted in abnormal sperm findings (reduced motility, reduced count, and increased percentage of abnormal sperm), and testes/epididymis organ changes (reduced weight and degeneration). Fertility was reduced in both treated males or females at the 275 mg/kg/day dose and reached statistical significance in males. Adverse changes in male and female reproductive organs also occurred in general 3-month and 6-month toxicology studies. In males, findings included spermatozoa degeneration at a belumosudil dose of 50 mg/kg/day in rats and 35 mg/kg/day in dogs. The exposure (AUC) at the doses of 50 mg/kg/day in male rats and 35 mg/kg/day in male dogs is approximately equivalent to the clinical exposure at the recommended dose of 200 mg/day. Changes were reversible in dogs but not fully reversible in rats. In female rats, changes included decreased follicular development in ovaries and lower uterine weights that correlated with uterine/cervical hypoplasia at 275 mg/kg/day [corresponding to 9 times exposure in patients at the recommended dose of 200 mg/day]. Changes were fully reversed during the 4-week recovery period.

14 CLINICAL STUDIES

14.1 Chronic Graft versus Host Disease

Study KD025-213 (NCT03640481) was a randomized, open-label, multicenter study of REZUROCK for treatment of patients with chronic GVHD who had received 2 to 5 prior lines of systemic therapy and required additional treatment. Patients were excluded from the studies if platelets were <50 × 10^9/L; absolute neutrophil count <1.5 × 10^9/L; AST or ALT >3 × ULN; total bilirubin >1.5 × ULN; QTc(F) >480 ms; eGFR <30 mL/min/1.73 m^2; or FEV1 ≤39%. There were 66 patients treated with REZUROCK 200 mg taken orally once daily. Concomitant treatment with supportive care therapies for chronic GVHD was permitted. Concomitant treatment with GVHD prophylaxis and standard care systemic chronic GVHD therapies was permitted as long as the subject has been on a stable dose for at least 2 weeks prior to study. Initiation of new systemic chronic GVHD therapy while on study was not permitted.

Demographics and baseline characteristics are summarized in Table 5.

Table 5: Demographics and Baseline Characteristics of Patients with Chronic GVHD
 | REZUROCK 200 mg once daily (N=65)
Age, Median, Years (minimum, maximum) | 53 (21, 77)
Age ≥65 Years, n (%) | 17 (26)
Male, n (%) | 42 (65)
Race, n (%)
White | 54 (83)
Black | 6 (9)
Other or Not Reported | 5 (8)
Median (range) time (months) from Chronic GVHD Diagnosis | 25.3 (1.9, 162.4)
≥4 Organs Involved, n (%) | 31 (48)
Median (range) Number of Prior Lines of Therapy | 3 (2, 6)
Number of Prior Lines of Therapy, n (%)
2 | 23 (35)
3 | 12 (19)
4 | 15 (23)
≥5 | 15 (23)
Prior chronic GVHD treatment with ibrutinib, n (%) | 21 (32)
Prior chronic GVHD treatment with ruxolitinib, n (%) | 20 (31)
Refractory to Last Therapy, n (% [Denominator excludes patients with unknown status]) | 43/55 (78)
Severe chronic GVHD, n (%) | 46 (71)
Median (range) Global Severity Rating | 7 (2, 9)
Median (range) Lee Symptom Scale Score at baseline | 27 (7, 56)
Median (range) Corticosteroid dose at baseline (PE/kg) [Prednisone equivalents/kilogram] | 0.19 (0.03, 0.95)

The efficacy of REZUROCK was based on overall response rate (ORR) through Cycle 7 Day 1 where overall response included complete response or partial response according to the 2014 NIH Response Criteria. The ORR results are presented in Table 6. The ORR was 75% (95% CI: 63, 85). The median duration of response, calculated from first response to progression, death, or new systemic therapies for chronic GVHD, was 1.9 months (95% CI: 1.2, 2.9). The median time to first response was 1.8 months (95% CI: 1.0, 1.9). In patients who achieved response, no death or new systemic therapy initiation occurred in 62% (95% CI: 46, 74) of patients for at least 12 months since response.

Table 6: Overall Response Rate through Cycle 7 Day 1 for Patients with Chronic GVHD in Study KD025-213
 | REZUROCK 200 mg once daily (N=65)
Overall Response Rate (ORR) | 49 (75%)
95% Confidence Interval [Estimated using Clopper-Pearson method] | (63%, 85%)
Complete Response | 4 (6%)
Partial Response | 45 (69%)

ORR results were supported by exploratory analyses of patient-reported symptom bother which showed at least a 7-point decrease in the Lee Symptom Scale summary score through Cycle 7 Day 1 in 52% (95% CI: 40, 65) of patients.

16 HOW SUPPLIED/STORAGE AND HANDLING

REZUROCK 200 mg tablets are supplied as pale yellow film-coated oblong tablets containing 200 mg of belumosudil (equivalent to 242.5 mg belumosudil mesylate). Each tablet is debossed with "KDM" on one side and "200" on the other side and is packaged as follows:

- 200 mg tablets in 30 count bottle: NDC 79802-200-30

STORAGE AND HANDLING

Store at room temperature, 20°C to 25°C (68°F to 77°F); excursions permitted from 15°C to 30°C (59°F to 86°F) [see USP Controlled Room Temperature].

Dispense to patient in original container only. Store in original container to protect from moisture. Replace cap securely each time after opening. Do not discard desiccant.

17 PATIENT COUNSELING INFORMATION

Advise the patient to read the FDA-approved patient labeling (Patient Information).

Embryo-fetal Toxicity:

- Advise pregnant women and females of reproductive potential of the potential risk to a fetus. Advise females of reproductive potential to inform their healthcare provider of a known or suspected pregnancy [see Warnings and Precautions (5.1), Use in Specific Populations (8.1, 8.3)].
- Advise females of reproductive potential to use effective contraceptive during treatment with REZUROCK and for one week after the last dose [see Warnings and Precautions (5.1)].
- Advise males with female partners of reproductive potential to use effective contraceptive during treatment with REZUROCK and for one week after the last dose [see Use in Specific Populations (8.3)].

Lactation

- Advise women not to breastfeed during treatment with REZUROCK and for one week after the last dose [see Use in Specific Populations (8.2)].

Infertility

- Advise males and females of reproductive potential that REZUROCK may impair fertility [see Use in Specific Populations (8.3)].

Administration

- Inform patients to take REZUROCK orally once daily with food according to their physician's instructions and that the oral dosage (tablets) should be swallowed whole with a glass of water, without cutting, crushing or chewing the tablets approximately the same time each day [see Dosage and Administration (2.1)].
- Advise patients that in the event of a missed daily dose of REZUROCK, it should be taken as soon as possible on the same day with a return to the normal schedule the following day. Patients should not take extra doses to make up the missed dose [see Dosage and Administration (2.1)].

Drug Interactions

- Advise patients to inform their health care providers of all concomitant medications, including prescription medicines, over-the-counter drugs, vitamins, and herbal products [see Drug Interactions (7)].

Distributed and marketed by:

Kadmon Pharmaceuticals, LLC
Morristown, NJ 07960
A SANOFI COMPANY
1-800-633-1610

REZUROCK® is a registered trademark of Kadmon Pharmaceuticals, LLC.
© 2025 Kadmon Pharmaceuticals, LLC. All rights reserved.

For patent information: https://www.sanofi.us/en/products-and-resources/patents

PATIENT INFORMATION
REZUROCK (REZ-ur-ok)
(belumosudil)
tablets

What is REZUROCK?

REZUROCK is a prescription medicine used to treat adults and children 12 years of age and older with chronic graft-versus-host disease (chronic GVHD) after you have received at least 2 prior treatments (systemic therapy) and they did not work.
It is not known if REZUROCK is safe and effective in children less than 12 years old.

Before taking REZUROCK, tell your healthcare provider about all of your medical conditions, including if you:

- have kidney or liver problems.
- are pregnant or plan to become pregnant. REZUROCK can harm your unborn baby. If you are able to become pregnant, your healthcare provider will do a pregnancy test before starting treatment with REZUROCK. Tell your healthcare provider if you become pregnant or think you may be pregnant during treatment with REZUROCK.
  - Females who can become pregnant should use effective birth control during treatment with REZUROCK and for 1 week after the last dose.
  - Males with female partners who can become pregnant should use effective birth control during treatment with REZUROCK and for 1 week after the last dose.
- are breastfeeding or plan to breastfeed. It is not known if REZUROCK passes into breast milk. Do not breastfeed during treatment with REZUROCK and for 1 week after the last dose.

Tell your healthcare provider about all the medicines you take, including prescription and over-the-counter medicines, vitamins, and herbal supplements. REZUROCK may affect the way other medicines work, and other medicines may affect the way REZUROCK works.
Know the medicines you take. Keep a list of them to show your healthcare provider and pharmacist when you get a new medicine.

How should I take REZUROCK?

- Take REZUROCK exactly as your healthcare provider tells you to take it.
- Do not change your dose or stop taking REZUROCK without first talking to your healthcare provider.
- Take REZUROCK 1 time a day with a meal.
- Take REZUROCK at about the same time each day.
- Swallow REZUROCK tablets whole with a glass of water.
- Do not cut, crush, or chew REZUROCK tablets.
- Your healthcare provider will do blood tests to check your liver at least 1 time a month during treatment with REZUROCK.
- If you miss a dose of REZUROCK, take it as soon as you remember on the same day. Take your next dose of REZUROCK at your regular time on the next day. Do not take extra doses of REZUROCK to make up for a missed dose.
- If you take too much REZUROCK, call your healthcare provider or go to the nearest hospital emergency room right away.

What are the possible side effects of REZUROCK?
The most common side effects of REZUROCK include:

- infections
- tiredness or weakness
- nausea
- diarrhea
- shortness of breath
- cough

- swelling
- bleeding
- stomach (abdominal) pain
- muscle or bone pain
- headache
- high blood pressure

Your healthcare provider may change your dose of REZUROCK, temporarily stop, or permanently stop treatment with REZUROCK if you have certain side effects.
REZUROCK may affect fertility in males and females. Talk to your healthcare provider if this is a concern for you.
These are not all the possible side effects of REZUROCK.
Call your doctor for medical advice about side effects. You may report side effects to FDA at 1-800-FDA-1088. You may also report side effects to Kadmon Pharmaceuticals, LLC at 1-800-633-1610.

How should I store REZUROCK?

- Store REZUROCK at room temperature between 68°F to 77°F (20°C to 25°C).
- Keep REZUROCK in its original container. The REZUROCK bottle contains a desiccant packet to help keep your tablets dry (protect from moisture). Keep the desiccant in the bottle.
- Tightly close the REZUROCK bottle after you take your dose.

Keep REZUROCK and all medicines out of the reach of children.

General information about the safe and effective use of REZUROCK.
Medicines are sometimes prescribed for purposes other than those listed in a Patient Information leaflet. Do not use REZUROCK for a condition for which it was not prescribed. Do not give REZUROCK to other people, even if they have the same symptoms that you have. It may harm them. You can ask your pharmacist or healthcare provider for information about REZUROCK that is written for health professionals.

What are the ingredients in REZUROCK?
Active ingredient: belumosudil mesylate
Inactive ingredients:
Tablet core: colloidal silicon dioxide, croscarmellose sodium, hypromellose, magnesium stearate, and microcrystalline cellulose.
Tablet coating: polyethylene glycol, polyvinyl alcohol, talc, titanium dioxide and yellow iron oxide.
Distributed and marketed by Kadmon Pharmaceuticals, LLC, Morristown, NJ 07960, A SANOFI COMPANY
REZUROCK® is a registered trademark of Kadmon Pharmaceuticals, LLC
© 2025 Kadmon Pharmaceuticals, LLC.
All rights reserved.
For more information, call 1-800-633-1610 or go to www.REZUROCK.com.

This Patient Information has been approved by the U.S. Food and Drug Administration

Revised: 4/2025

PRINCIPAL DISPLAY PANEL - 200 mg Tablet Bottle Carton

NDC 79802-200-30
Rx only

REZUROCK®
(belumosudil) tablets

200 mg

Swallow tablets whole. Do not cut,
crush, or chew the tablets.

30 Tablets

sanofi